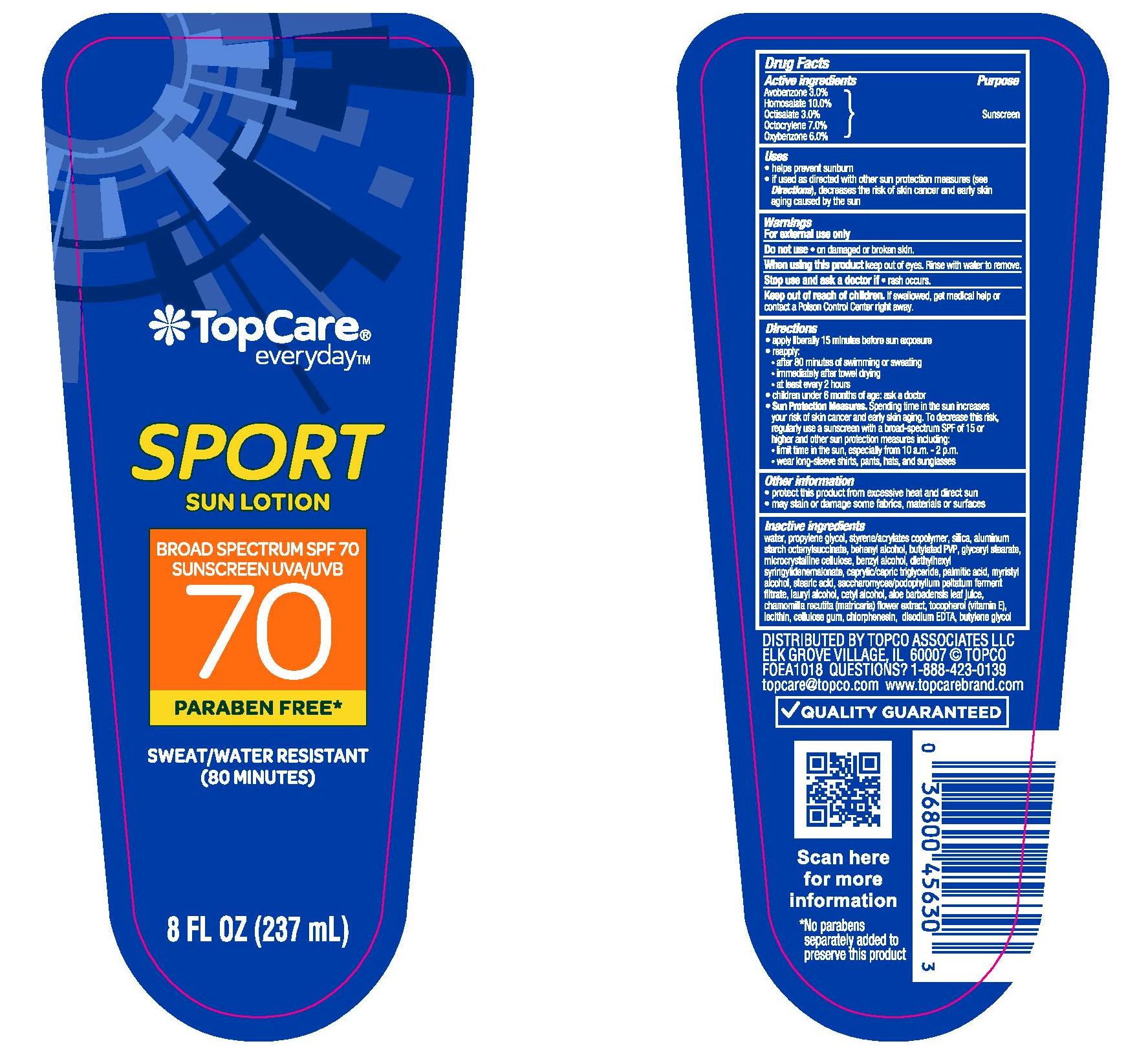 DRUG LABEL: TOPCARE EVERYDAY SPORT SPF 70 SUNSCREEN
NDC: 36800-940 | Form: LOTION
Manufacturer: TOPCO ASSOCIATES LLC
Category: otc | Type: HUMAN OTC DRUG LABEL
Date: 20241015

ACTIVE INGREDIENTS: OCTOCRYLENE 70 mg/1 mL; AVOBENZONE 30 mg/1 mL; HOMOSALATE 100 mg/1 mL; OCTISALATE 30 mg/1 mL; OXYBENZONE 60 mg/1 mL
INACTIVE INGREDIENTS: PODOPHYLLUM PELTATUM ROOT; BUTYL METHACRYLATE/METHYL METHACRYLATE/METHACRYLIC ACID/STYRENE CROSSPOLYMER; CARBOXYMETHYLCELLULOSE SODIUM, UNSPECIFIED FORM; BENZYL ALCOHOL; STEARIC ACID; LAURYL ALCOHOL; EDETATE DISODIUM; CHAMOMILE; DIETHYLHEXYL SYRINGYLIDENEMALONATE; WATER; DOCOSANOL; MICROCRYSTALLINE CELLULOSE; .ALPHA.-TOCOPHEROL, DL-; LECITHIN, SOYBEAN; CHLORPHENESIN; BUTYLENE GLYCOL; SILICON DIOXIDE; GLYCERYL MONOSTEARATE; ALOE VERA LEAF; PROPYLENE GLYCOL; ALUMINUM STARCH OCTENYLSUCCINATE; MEDIUM-CHAIN TRIGLYCERIDES; PALMITIC ACID; MYRISTYL ALCOHOL; CETYL ALCOHOL

TOPCARE EVERYDAY SPORT SPF 70 SUN LOTION

Active ingredients

Avobenzone 3.0%, Homosalate 10.0%, Octisalate 3.0%, Octocrylene 7.0%, Oxybenzone 6.0%

Purpose

Sunscreen

Uses

- helps prevent sunburn
- if used as directed with other sun protection mesaures (see Directions), decreases the risk of skin cancer and early skin aging caused by the sun

Warnings

For external use only

Do not use

- on damaged or broken skin.

When using this product

- keep out of eyes. Rinse with water to remove.

Stop use and ask a doctor if

- rash occurs.

Keep out of reach of children.

If swallowed, get medical help or contact a Poison Control Center right away.

Directions

- apply liberally 15 minutes before sun exposure
- reapply:
- after 80 minutes of swimming or sweating
- immediately after towel drying
- at least every 2 hours
- children under 6 months of age: Ask a doctor
- Sun Protection Measures. Spending time in the sun increases your risk of skin cancer and early skin aging. To decrease this risk, regularly use a sunscreen with a Broad Spectrum SPF value of 15 or higher and other sun protection measures including:
- limit time in the sun, especially from 10 a.m.-2 p.m.
- wear long-sleeved shirts, pants, hats, and sunglasses

Other information

- protect the product in this container from excessive heat and direct sun
- may stain or damage some fabrics, materials or surfaces

Inactive ingredients

water, propylene glycol, styrene/acrylates copolymer, silica, aluminum starch octenylsuccinate, behenyl alcohol, butylated PVP, glyceryl stearate, microcrystalline cellulose, benzyl alcohol, diethylhexyl syringylidenemalonate, caprylic/capric triglyceride, palmitic acid, myristyl alcohol, stearic acid, saccharomyces/podophyllum peltatum ferment filtrate, lauryl alcohol, cetyl alcohol, aloe barbadensis leaf juice, chamomilla recutita (matricaria) flower extract, tocopherol (vitamin E), lecithin, cellulose gum, chlorphenesin, disodium EDTA, butylene glycol

PACKAGE LABEL

TOPCARE EVERYDAY SPORT SPF 70 SUN LOTION

8 FL OZ. (237mL)

NDC 36800-940-11